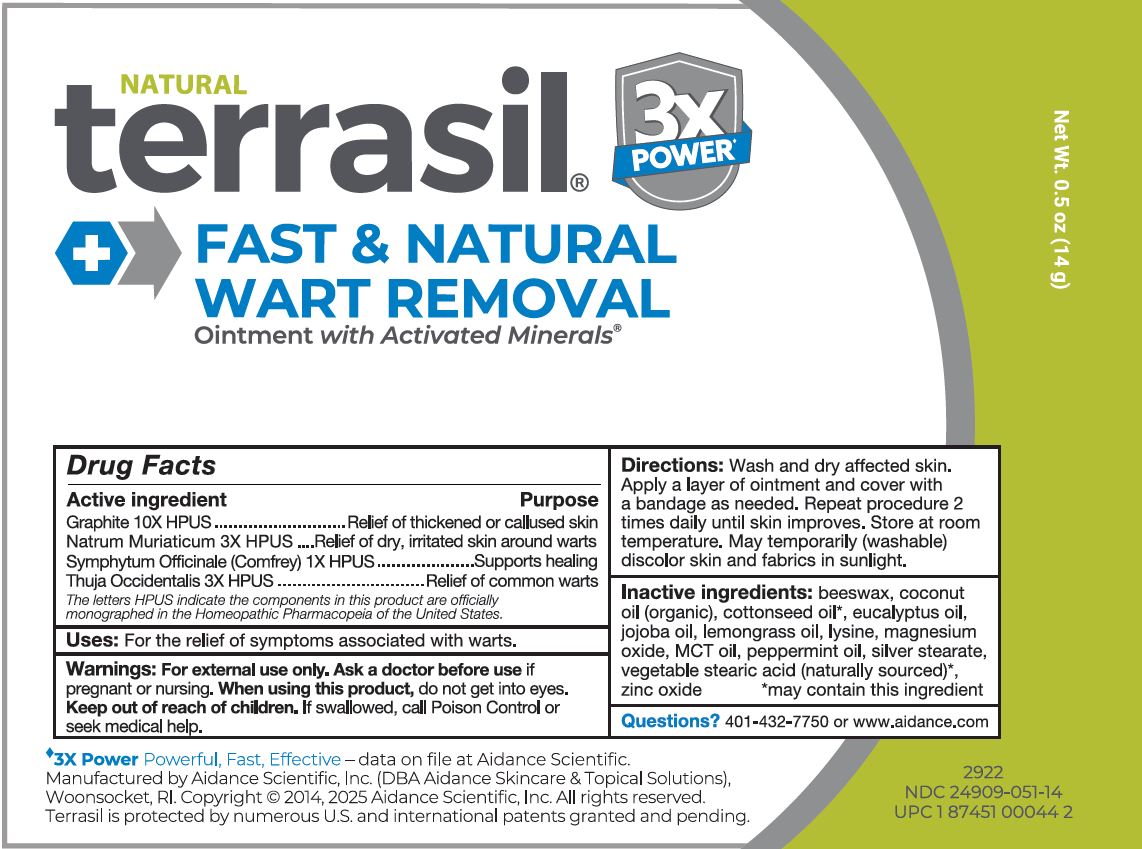 DRUG LABEL: terrasil Fast and Natural Wart Removal
NDC: 24909-051 | Form: OINTMENT
Manufacturer: Aidance Scientific, Inc.
Category: homeopathic | Type: HUMAN OTC DRUG LABEL
Date: 20250825

ACTIVE INGREDIENTS: SODIUM CHLORIDE 3 [hp_X]/1 g; SYMPHYTUM OFFICINALE WHOLE 1 [hp_X]/1 g; THUJA OCCIDENTALIS LEAFY TWIG 3 [hp_X]/1 g; GRAPHITE 10 [hp_X]/1 g
INACTIVE INGREDIENTS: COCONUT OIL; JOJOBA OIL; COTTONSEED OIL; BEESWAX; EUCALYPTUS OIL; STEARIC ACID; LEMONGRASS OIL; LYSINE; PALM OIL; PEPPERMINT OIL; SILVER STEARATE; MAGNESIUM OXIDE; ZINC OXIDE

24909-051 terrasil Fast & Natural Wart Removal

Active Ingredients

Graphite 10X HPUS, Natrum Muriaticum 3X HPUS, Symphytum Officinale (Comfrey) 1X HPUS, Thuja Occidentalis 3X HPUS

Purpose

Graphite 10X HPUS .........................................Relief of thickened or callused skin
Natrum Muriaticum 3X HPUS ..........................Relief of dry, irritated skin around warts
Symphytum Officinale (Comfrey) 1X HPUS.....Supports healing
Thuja Occidentalis 3X HPUS ..........................Relief of common warts

The letters HPUS indicate the components in this product are officially monographed in the Homeopathic Pharmacopeia of the United States.

Uses

For the relief of symptoms associated with warts.

Warnings

For external use only. Ask a doctor before use if pregnant or nursing. When using this product, do not get into eyes.

Keep out of reach of children.

OTHER SAFETY INFORMATION

If swallowed, call Poison Control or seek medical help.

Directions

Wash and dry affected skin. Apply a layer of ointment and cover with a bandage as needed. Repeat procedure 2 times daily until skin improves. Store at room temperature. May temporarily (washable) discolor skin and fabrics in sunlight.

Inactive Ingredients

beeswax, coconut oil (organic), cottonseed oil*, eucalyptus oil, jojoba oil, lemongrass oil, lysine, magnesium oxide, MCT oil, peppermint oil, silver stearate, vegetable stearic acid (naturally sourced)*, zinc oxide

*may contain this ingredient

Questions?

401-432-7750 or www.aidance.com

Homeopathic Medicine